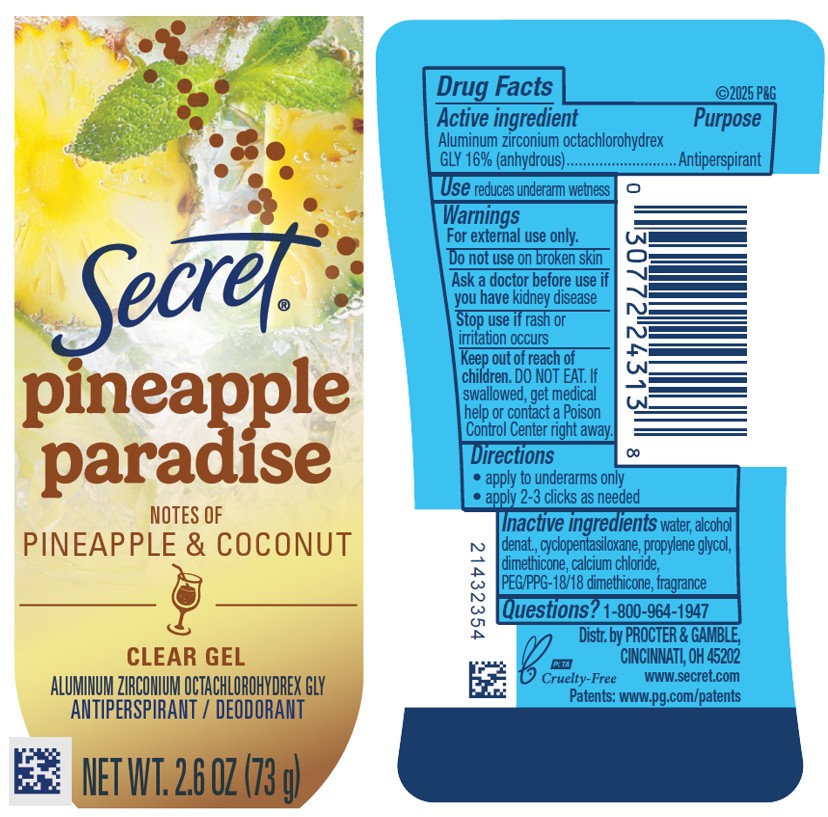 DRUG LABEL: Secret Pineapple Paradise Clear
NDC: 84126-223 | Form: GEL
Manufacturer: The Procter & Gamble Manufacturing Company
Category: otc | Type: HUMAN OTC DRUG LABEL
Date: 20260220

ACTIVE INGREDIENTS: ALUMINUM ZIRCONIUM OCTACHLOROHYDREX GLY 16 g/100 g
INACTIVE INGREDIENTS: PEG/PPG-18/18 DIMETHICONE; CALCIUM CHLORIDE; WATER; ALCOHOL; CYCLOPENTASILOXANE; PROPYLENE GLYCOL; DIMETHICONE

Secret Pineapple Paradise Clear

Drug Facts

Active ingredient

Aluminum zirconium octachlorohydrex Gly 16% (anhydrous)

Purpose

Antiperspirant

Use

reduces underarm wetness

Warnings

For external use only.

Do not use on broken skin

Ask a doctor before use if you have kidney disease

Stop use if rash or irritation occurs

Keep out of reach of children. If swallowed, get medical help or contact a Poison Control Center right away.

Directions

- apply to underarms only
- apply 2-3 clicks as needed

Inactive ingredients

Water, alcohol denat., cyclopentasiloxane, propylene glycol, dimethicone, calcium chloride, PEG/PPG-18/18 dimethicone, fragrance

Questions?

1-800-964-1947

Dist. By PROCTER & GAMBLE,
CINCINNATI, OH 45202.

PRINCIPAL DISPLAY PANEL - 73 g Cylinder Label

Secret

pineapple

paradise

NOTES OF

PINEAPPLE & COCONUT

CLEAR GEL

ALUMINUM ZIRCONIUM OCTACHLOROHYDREX GLY

ANTIPERSPIRANT / DEODORANT

NET WT. 2.6 OZ (73 g)